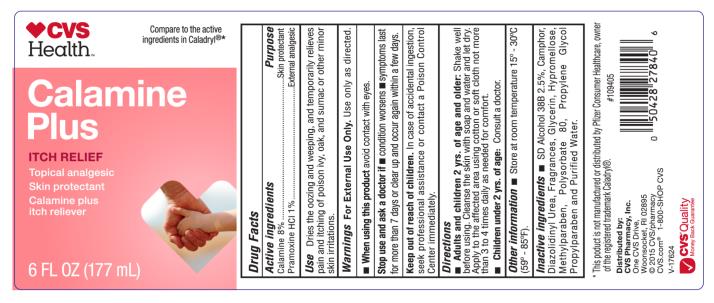 DRUG LABEL: CVS Calamine Plus
NDC: 69842-420 | Form: LOTION
Manufacturer: CVS Pharmacy
Category: otc | Type: HUMAN OTC DRUG LABEL
Date: 20231222

ACTIVE INGREDIENTS: ZINC OXIDE 80 mg/1 mL; PRAMOXINE HYDROCHLORIDE 10 mg/1 mL
INACTIVE INGREDIENTS: ALCOHOL; CAMPHOR (SYNTHETIC); DIAZOLIDINYL UREA; GLYCERIN; HYPROMELLOSES; METHYLPARABEN; POLYSORBATE 80; PROPYLENE GLYCOL; PROPYLPARABEN; WATER

CVS Calamine Plus

CVS Calamine Plus

Drug Facts

Active Ingredient

Calamine 8%

Active Ingredient

Pramoxine HCl 1%

Purpose

Skin Protectant

Purpose

External Analgesic

Use

Dries the oozing and weeping, and temporarily relieves pain and itching of poison ivy, oak, and sumac or other minor skin irritations.

Warnings

For external use only. Use only as directed.

Stop use and ask a doctor if

- condition worsens
- symptoms last for more than 7 days or clear up and occur again within a few days.

Keep out of reach of children.

- In case of accidental ingestion, seek professional assistance or contact a Poison Control Center immediately.

Directions

- Adults and children 2 yrs. of age and older. Shake well before using. Cleanse the skin with soap and water and let dry. Apply to the affected area using cotton or soft cloth not more than 3 to 4 times daily as needed for comfort.
- Children under 2 yrs. of age: Consult a doctor.

Other Information

- store at room temperature 15o – 30oC (59o – 85oF)

Inactive Ingredient

SD Alcohol 38B 2.5%, Camphor, Diazolidinyl Urea, Fragrances, Glycerin, Hypromellose, Methylparaben, Polysorbate 80, Propylene Glycol, Propylparaben, and Purified Water.

PRINCIPAL DISPLAY PANEL

Calamine
Plus
Itch Relief
6 FL OZ (177 mL)